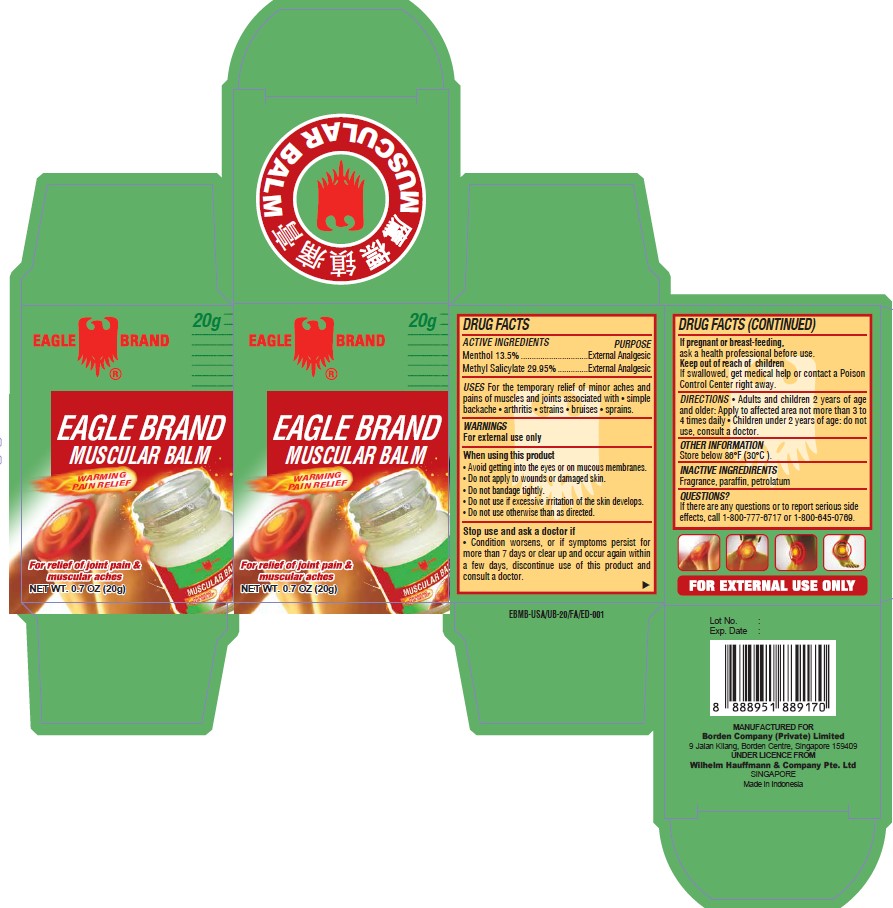 DRUG LABEL: Eagle Brand
NDC: 60954-200 | Form: OINTMENT
Manufacturer: PT. EAGLE INDO PHARMA
Category: otc | Type: HUMAN OTC DRUG LABEL
Date: 20260105

ACTIVE INGREDIENTS: METHYL SALICYLATE 29.95 g/100 g; MENTHOL 13.5 g/100 g
INACTIVE INGREDIENTS: PARAFFIN; PETROLATUM

Eagle Brand Muscular Balm

Active Ingredients

- Menthol 13.5%
- Methyl Salicylate 29.95%

Purpose

External Analgesic

Uses

For the temporary relief of minor aches and pains of muscles and joints associated with • simple backache • arthritis • strains • bruises • sprains.

Warnings

For external use only

When using this product

- Avoid getting into the eyes or mucous membranes.
- Do not apply to wounds or damaged skin.
- Do not bandage tightly.
- Do not use if excessive irritation of the skin develops.
- Do not use otherwise than as directed.

Stop use and ask doctor if

Condition worsens, or if symptoms persist for more than 7 days or clear up and occur again within a few days, discontinue use of this product and consult a doctor.

If pregnant or breast-feeding

Ask a health professional before use.

Keep out of reach of children

If swallowed, get medical help or contact a Poison Control Centre right away.

Directions

- Adults and children 2 years of age and older: Apply to affected area not more than 3 to 4 times daily.
- Children under 2 years of age: do not use, consult a doctor.

Other information

Store below 86oF (30oC).

Inactive ingredients

Fragrance, paraffin, petrolatum.

Questions?

If there are any questions or to report serious side effects, call 1-800-777-6717 or 1-800-645-0769.

Package Label

20g NDC: 60954-200-20